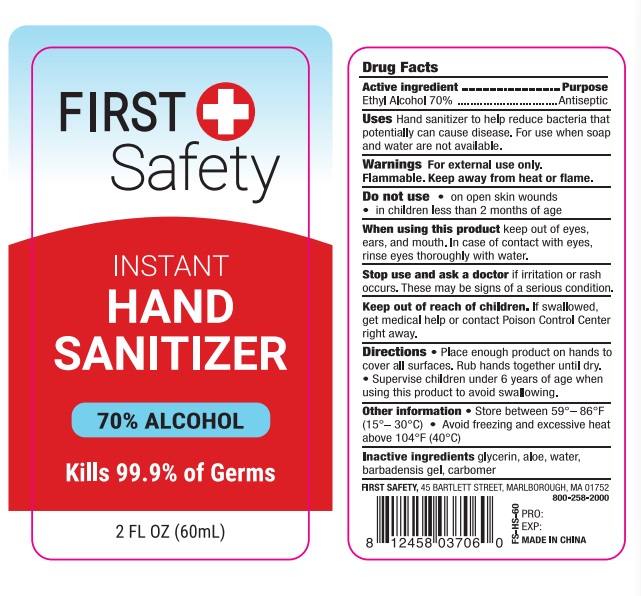 DRUG LABEL: First Safety Instant Hand Sanitizer
NDC: 75780-008 | Form: GEL
Manufacturer: Ningbo Mannike Biological Technology Co., Ltd.
Category: otc | Type: HUMAN OTC DRUG LABEL
Date: 20200515

ACTIVE INGREDIENTS: alcohol 70 mL/100 mL
INACTIVE INGREDIENTS: WATER; PROPYLENE GLYCOL; ALOE VERA LEAF; CARBOMER 934; GLYCERIN

Drug facts

Active ingredient Purpose

Ethyl Alcohol 70% ... Antiseptic

PURPOSE

Hand sanitizer to help reduce bacteria that potentially can cause disease. For use when soap and water are not available.

KEEP OUT OF REACH OF CHILDREN

If swallowed, get meical help or contact Poison Control Center right away.

INDICATIONS AND USAGE

keep out of eyes,ears, and mouth. In case of contact with eyes, rinse eyes thoroughly with water.

Stop use and ask a doctor, if irritation or rash occurs. These may be signs of a serious condition.

WARNINGS

For external use only.
Flammable. Keep away from heat or flame.

Do not use:

- On open skin wounds
- in children less than 2 months of age

DOSAGE AND ADMINISTRATION

- Place enough product on hands to cover all surfaces. Rub hands together until dry.
- Supervise children under 6 years of age when using this product to avoid swallowing.

Other information:

- Store between 59°-86℉ （15°-30℃）
- Avoid freezing and excessive heat above 104℉ （40℃）

INACTIVE INGREDIENT

Glycerin, Aloe， water, Barbadensis gel, Carbomer